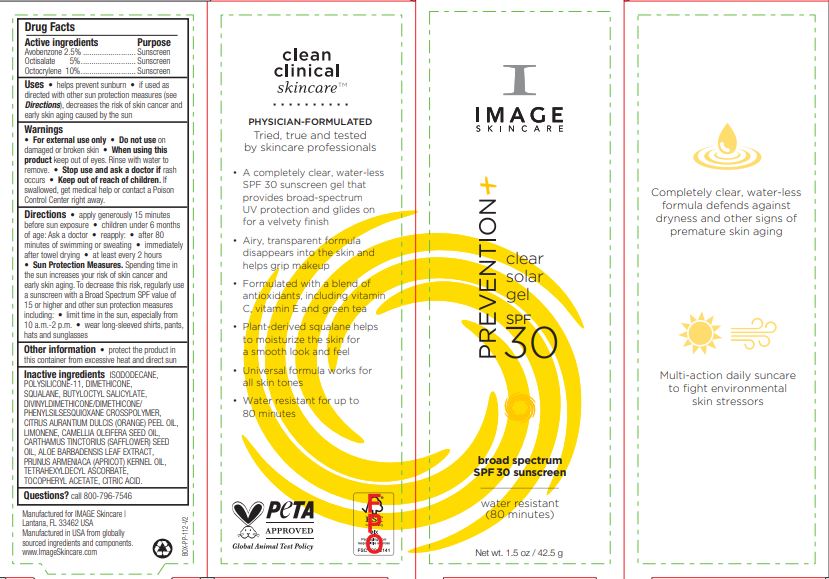 DRUG LABEL: Prevention Clear Solar Gel SPF30
NDC: 62742-4226 | Form: CREAM
Manufacturer: Allure LAbs
Category: otc | Type: HUMAN OTC DRUG LABEL
Date: 20241209

ACTIVE INGREDIENTS: AVOBENZONE 2.5 g/100 g; OCTISALATE 5 g/100 g; OCTOCRYLENE 10 g/100 g
INACTIVE INGREDIENTS: LIMONENE, (+)-; SAFFLOWER OIL; ALOE VERA LEAF; TETRAHEXYLDECYL ASCORBATE; CITRIC ACID MONOHYDRATE; ISODODECANE; DIMETHICONE/VINYL DIMETHICONE CROSSPOLYMER (SOFT PARTICLE); .ALPHA.-TOCOPHEROL ACETATE; SQUALANE; BUTYLOCTYL SALICYLATE; DIMETHICONE/DIVINYLDIMETHICONE/SILSESQUIOXANE CROSSPOLYMER; CAMELLIA OIL; DIMETHICONE; APRICOT KERNEL OIL; ORANGE OIL

Drug Facts

Active ingredients

Avobenzone 2.5%

Octisalate 5%

Octocrylene 10%

Purpose

Sunscreen

Uses

Helps prevent sunburn • if used as directed with other sun protection measures (see Directions), decreases the risk of skin cancer and early skin aging caused by the sun

Warnings

For external use only

Do not use on damaged or broken skin

When using this product keep out of eyes. Rinse with water to remove.

Stop use and ask a doctor if rash occurs

Keep out of reach of children. If swallowed, get medical help or contact a Poison Control Center right away.

DOSAGE AND ADMINISTRATION

Directions • apply generously 15 minutes before sun exposure • children under 6 months of age: Ask a doctor • reapply: • after 80 minutes of swimming or sweating • immediately after towel drying • at least every 2 hours • Sun Protection Measures. Spending time in the sun increases your risk of skin cancer and early skin aging. To decrease this risk, regularly use a sunscreen with a Broad Spectrum SPF value of 15 or higher and other sun protection measures including: • limit time in the sun, especially from 10 a.m.-2 p.m. • wear long-sleeved shirts, pants, hats and sunglasses

Other information • protect the product in this container from excessive heat and direct sun

INACTIVE INGREDIENT

Inactive ingredients ISODODECANE, POLYSILICONE-11, DIMETHICONE, SQUALANE, BUTYLOCTYL SALICYLATE, DIVINYLDIMETHICONE/DIMETHICONE/ PHENYLSILSESQUIOXANE CROSSPOLYMER, CITRUS AURANTIUM DULCIS (ORANGE) PEEL OIL, LIMONENE, CAMELLIA OLEIFERA SEED OIL, CARTHAMUS TINCTORIUS (SAFFLOWER) SEED OIL, ALOE BARBADENSIS LEAF EXTRACT, PRUNUS ARMENIACA (APRICOT) KERNEL OIL, TETRAHEXYLDECYL ASCORBATE, TOCOPHERYL ACETATE, CITRIC ACID.